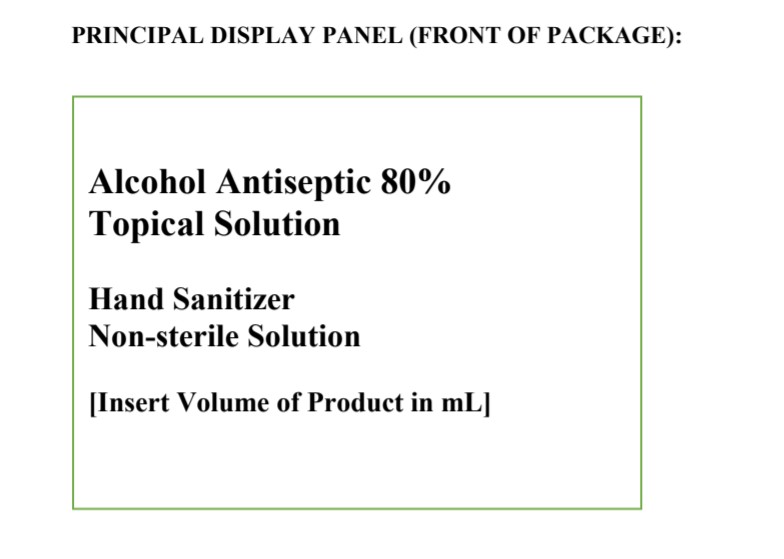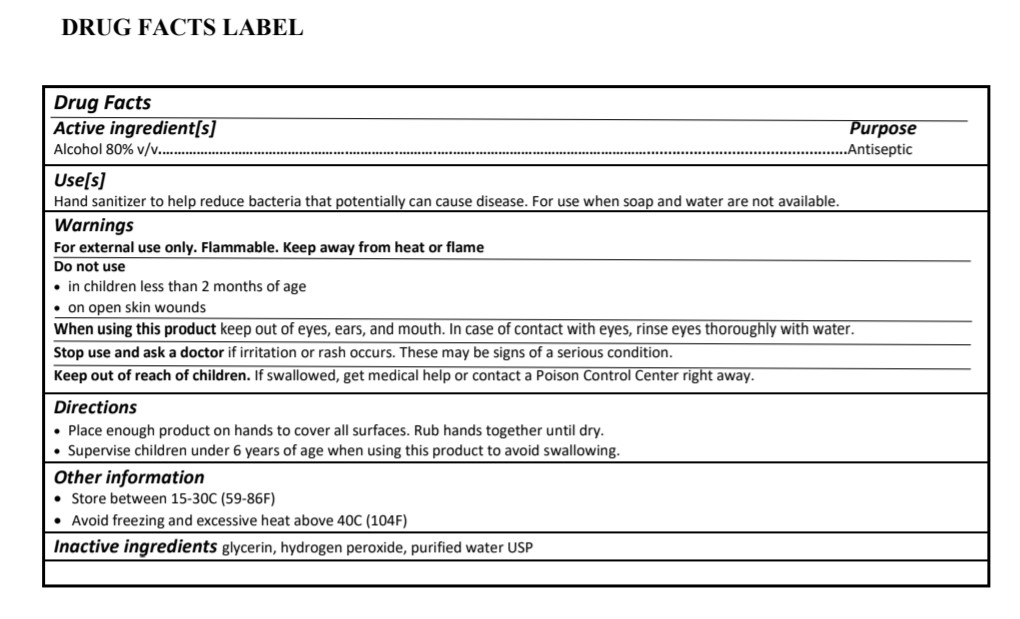 DRUG LABEL: Hand Sanitizer
NDC: 73995-100 | Form: LIQUID
Manufacturer: Barley Creek Associates, L.P.
Category: otc | Type: HUMAN OTC DRUG LABEL
Date: 20200327

ACTIVE INGREDIENTS: ALCOHOL 80 mL/100 mL
INACTIVE INGREDIENTS: GLYCERIN; WATER; HYDROGEN PEROXIDE

STORAGE AND HANDLING

Store between 15-30C (59-86F)
Avoid freezing and excessive heat above 40C (104F)

Directions

Place enough product on hands to cover all surfaces. Rub hands together until dry.
Supervise children under 6 years of age when using this product to avoid swallowing.

GENERAL PRECAUTIONS

For external use only. Flammable. Keep away from heat or flame

Do not use

In children less than 2 months of age
On open skin wounds

When using this product keep out of eyes, ears, and mouth. In case of contact with eyes, rinse eyes thoroughly with water.

Stop use and ask a doctor if irritation or rash occurs. These may me signs of a serious condition.

Keep out of reach of children. If swallowed, get medical help or contact a Poison Control Center right away.

Inactive ingredients glycerin, hydrogen peroxide, purified water USP

Purpose - Antiseptic

Use(s) Hand sanitizer to help reduce bacteria that potentially can cause disease. For use when soap and water are not available.

Active ingredient(s) - Alcohol 80% v/v

Keep out of reach of children. If swallowed, get medical help or contact a Poison Control Center right away.

Do not use

In children less than 2 months of age
On open skin wounds

Directions

Place enough product on hands to cover all surfaces. Rub hands together until dry.
Supervise children under 6 years of age when using this product to avoid swallowing.

INDICATIONS AND USAGE

Use(s) Hand sanitizer to help reduce bacteria that potentially can cause disease. For use when soap and water are not available.

Warnings

For external use only. Flammable. Keep away from heat or flame

Do not use

In children less than 2 months of age
On open skin wounds

When using this product keep out of eyes, ears, and mouth. In case of contact with eyes, rinse eyes thoroughly with water.

Stop use and ask a doctor if irritation or rash occurs. These may me signs of a serious condition.

Keep out of reach of children. If swallowed, get medical help or contact a Poison Control Center right away.